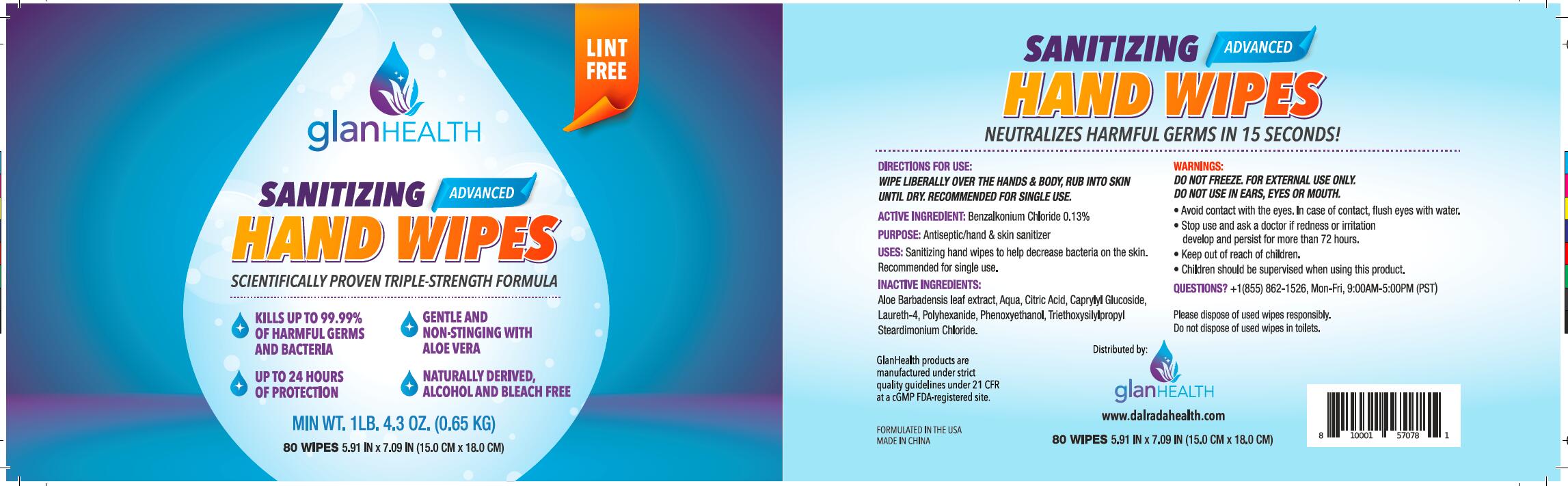 DRUG LABEL: Sanitizing Hand wipes
NDC: 51706-907 | Form: CLOTH
Manufacturer: Landy International
Category: otc | Type: HUMAN OTC DRUG LABEL
Date: 20200531

ACTIVE INGREDIENTS: BENZALKONIUM CHLORIDE 0.13 g/100 g
INACTIVE INGREDIENTS: TRIETHOXY(3-ISOCYANATOPROPYL)SILANE; PHENOXYETHANOL; CITRIC ACID MONOHYDRATE; WATER; CAPRYLYL GLUCOSIDE; LAURETH-4; POLIHEXANIDE; ALOE VERA LEAF; TRIMETHYL OCTADECYL AMMONIUM CHLORIDE

51706-907 Sanitizing wipes 0.13% Benzalkonium Chloride

Active Ingredient(s)

Benzalkonium Chloride 0.13%

Purpose

Antiseptic/Hand & Skin Sanitizer

Use

Sanitizing Hand Wipes to help decrease bacteria on the skin.
Recommended for single use.

Warnings

Do not freeze. For external use only.
Do not use in ears, eyes or mouth.
●Avoid contact with the eyes. In case of contact, flush eyes with water.
●Stop use and ask a doctor if redness or iritation
develop and persist for more than 72 hours.
●Keep out of reach of children.
●Children should be supervised when using this product.

Keep out of reach of children.

Directions

Wipe liberally over the hands & body, rub into skin until dry.
Recommended for single use.

Inactive ingredients

Aloe Barbadensis leaf extract, Aqua, Citric Acid, CaprylyI Glucoside,
Laureth-4, Polyhexanide, Phenoxyethanol, Triethoxysilylpropyl
Steardimonium Chloride.